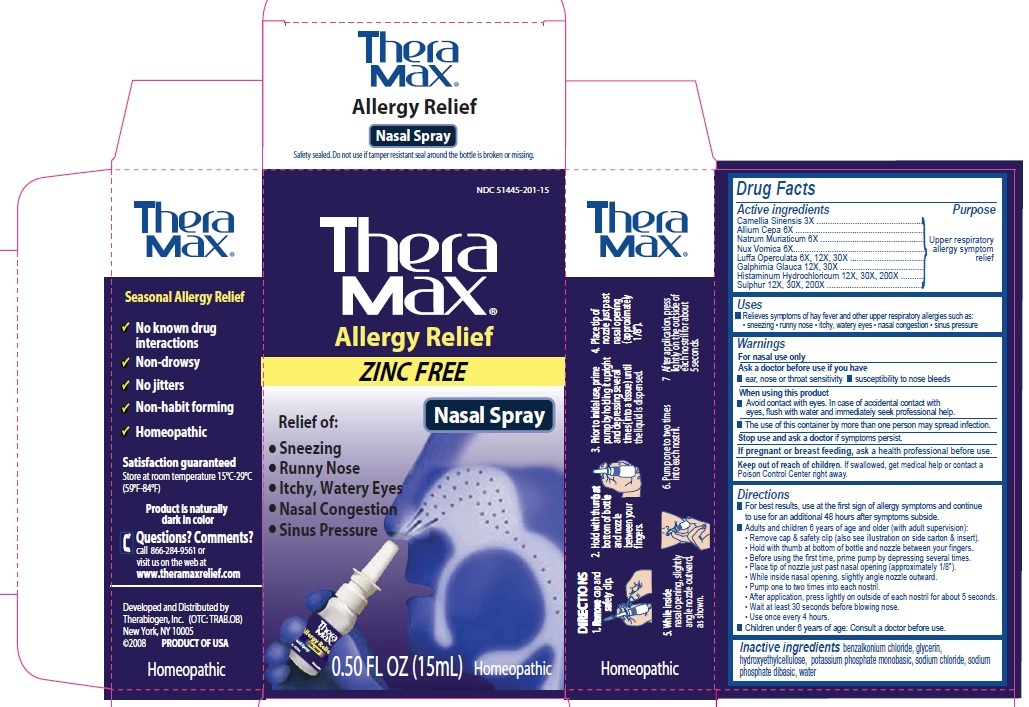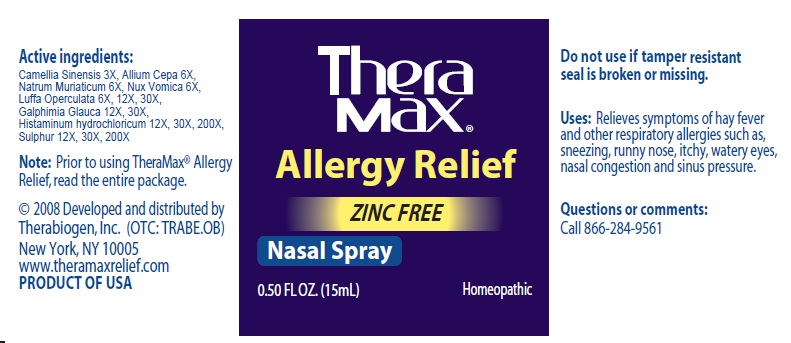 DRUG LABEL: THERAMAX ALLERGY RELIEF NASAL
NDC: 51445-201 | Form: SPRAY
Manufacturer: THERABIOGEN
Category: homeopathic | Type: HUMAN OTC DRUG LABEL
Date: 20101006

ACTIVE INGREDIENTS: GREEN TEA LEAF 3 [hp_X]/15 mL; ONION 6 [hp_X]/15 mL; SODIUM CHLORIDE 6 [hp_X]/15 mL; STRYCHNOS NUX-VOMICA SEED 6 [hp_X]/15 mL; LUFFA OPERCULATA FRUIT 6 [hp_X]/15 mL; GALPHIMIA GLAUCA FLOWERING TOP 12 [hp_X]/15 mL; HISTAMINE DIHYDROCHLORIDE 12 [hp_X]/15 mL; SULFUR 12 [hp_X]/15 mL
INACTIVE INGREDIENTS: BENZALKONIUM CHLORIDE; GLYCERIN; POTASSIUM PHOSPHATE, MONOBASIC; SODIUM CHLORIDE; SODIUM PHOSPHATE, DIBASIC; WATER

THERAMAX ALLERGY RELIEF ZINC FREE NASAL SPRAY

Drug Facts

Active Ingredients Purpose

Camellia Sinensis 3X Upper respiratory allergy symptom relief

Allium Cepa 6X Upper respiratory allergy symptom relief

Natrum Muriaticum 6X Upper respiratory allergy symptom relief

Nux Vomica 6X Upper respiratory allergy symptom relief

Luffa Oprculata 6X, 12X, 30X Upper respiratory allergy symptom relief

Galphimia Glauca 12X, 30X Upper respiratory allergy symptom relief

Histaminum Hydrochloricum 12X, 30X, 200X Upper respiratory allergy symptom relief

Sulphur 12X, 30X, 200X Upper respiratory allergy symptom relief

Purpose:

Upper respiratory allergy symptom relief

Uses

Relieves symptoms of hay fever and other upper respiratory allergies such as:

sneezing runny nose itchy, watery eyes nasal congestion sinus pressure

Warnings

For nasal use only.

Ask a doctor before use if you have

ear nose or throat sensitivity

susceptibility to nose bleeds

When using this product

Avoid contact with eyes. In case of accidental contact with eyes, flush with water and immediately seek professional help.

The use of this container by more than one person may spread infection.

Stop use and ask a doctor if symptoms persist

PREGNANCY OR BREAST FEEDING

If pregnant or breast feeding, ask a health professional before use.

Keep out of reach of children. If swallowed, get medical help or contact a Poison Control Center right away.

Directions

For best results, use at the first sign of allergy symptoms and continue to use for an additional 48 hours after symptoms subside.

Adults and children 6 years of age and older (with adult supervision):

Remove cap and safety clip (also see illustration on side carton and insert)

Hold with thumb at bottom of bottle and nozzle between your fingers. Before using the first time, prime pump by depressing several times.

Place tip of nozzle just past nasal opening (approximately 1/8")

While inside nasal opening, slightly angle nozzle outward.

Pump one to two times into each nostril

After application, press lightly on outside of each nostril for about 5 seconds.

Wait at least 30 seconds before blowing nose

Use once every 4 hours

Children under 6 years of age: Consult a doctor before use.

Inactive Ingredients

Benzalkonium chloride, glycerin, hydroxyethylcellulose, potassium phosphate monobasic, sodium chloride, sodium phosphate dibasic, water

PACKAGE LABEL

THERAMAX NDC 51445-201-15

Seasonal Allergy Relief

No known drug interactions

Non-drowsy

No jitters

Non-habit forming

Homeopathic

Satisfaction Guaranteed

Store at room temperature 15C-29C (59F-84F)

Product is naturally dark in color

Questions? Comments?

call 866-284-9561 or visit us on the web at

www. theramaxrelief.com

Developed and distributed by Therabiogen, Inc. (OTC: TRAB.OB)

(c)2008 Product of USA

HOMEOPATHIC

THERAMAX

ALLERGY RELIEF

ZINC FREE

NASAL SPRAY

Relief of

Sneezing

Runny Nose

Itchy, Watery Eyes

Nasal Congestion

Sinus Pressure

0.50 FL OZ (15ml) Homeopathic

DIRECTIONS

1. Remove cap and safety clip

2. Hold with thumb at bottom of bottle and nozzle between your fingers

3. Prior to initial use, prime pump by holding it upright and depressing several times (into a tissue) until the liquid is dispensed.

4. Place tip of nozzle just past nasal opening (approximately 1/8")

5. While inside nasal opening, slightly angle nozzle outward as shown

6. Pump one to two times into each nostril

7. After application, press lightly on the outside of each nostril for about 5 seconds.

HOMEOPATHIC

PACKAGE LABEL

Active Ingredients:

Camellia Sinensis 3X, Allium cepa 6X

Natrum Muriaticum 6X, Nux vornica 6X

Luffa Operculata 6X, 12X, 30X

Galphimia Glauca 12X, 30X

Histaminum Hydrochloricum 12X, 30X, 200X

Sulphur 12X, 30X, 200X

Note: Prior to using Theramax Allergy Relief, read the entire package

(c) Developed and distributed by Therabiogen, Inc. (OTC: TRABE.OB)

New York, NY 10005

www.theramaxrelief.com

PRODUCT OF USA

Theramax

Allergy Relief

Zinc Free

Nasal Spray

0.50 FL OZ. (15ml) HOMEOPATHIC

Do not use if tamper resistant seal is broken or missing.

Uses: Relieves symptoms of hay fever and other respiratory allergies such as, sneezing, runny nose, itchy watery eyes, nasal congestion and sinus pressure.

Questions or comments: Call 866-284-9561